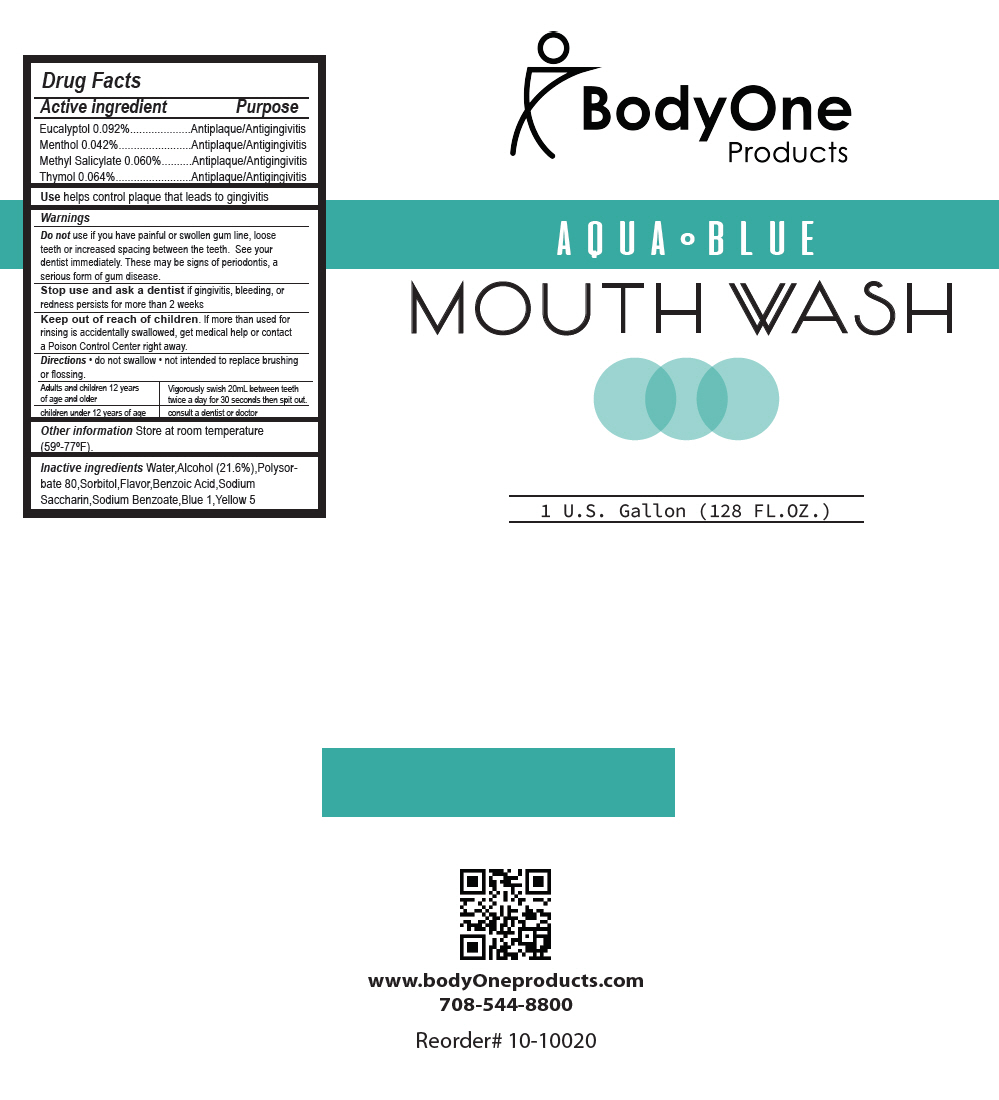 DRUG LABEL: Aqua Blue Mouthwash
NDC: 73563-022 | Form: LIQUID
Manufacturer: Body One Products Inc
Category: otc | Type: HUMAN OTC DRUG LABEL
Date: 20200227

ACTIVE INGREDIENTS: Methyl Salicylate 0.6 mg/1 mL; MENTHOL, UNSPECIFIED FORM 0.42 mg/1 mL; Eucalyptol 0.92 mg/1 mL; Thymol 0.64 mg/1 mL
INACTIVE INGREDIENTS: Water; alcohol 216 mg/1 mL; SORBITOL; Benzoic Acid; SACCHARIN SODIUM; Sodium Benzoate; Polysorbate 80; FD&C Blue No. 1; FD&C Yellow No. 5

Aqua Blue Mouthwash

Drug Facts

ACTIVE INGREDIENT

Active ingredient | Purpose
Eucalyptol 0.092% | Antiplaque/Antigingivitis
Menthol 0.042% | Antiplaque/Antigingivitis
Methyl Salicylate 0.060% | Antiplaque/Antigingivitis
Thymol 0.064% | Antiplaque/Antigingivitis

Use

helps control plaque that leads to gingivitis

Warnings

Do not use if you have painful or swollen gum line, loose teeth or increased spacing between the teeth. See your dentist immediately. These may be signs of periodontis, a serious form of gum disease.

Stop use and ask a dentist if gingivitis, bleeding, or redness persists for more than 2 weeks

Keep out of reach of children. If more than used for rinsing is accidentally swallowed, get medical help or contact a Poison Control Center right away.

Directions

- do not swallow
- not intended to replace brushing or flossing.

Adults and children 12 years of age and older | Vigorously swish 20mL between teeth twice a day for 30 seconds then spit out.
children under 12 years of age | consult a dentist or doctor

Other information

Store at room temperature (59°-77°F).

Inactive ingredients

Water,Alcohol (21.6%),Polysorbate 80,Sorbitol,Flavor,Benzoic Acid,Sodium Saccharin,Sodium Benzoate,Blue 1,Yellow 5

PRINCIPAL DISPLAY PANEL - 128 FL.OZ. Jug Label

BodyOne
Products

AQUA ⚬ BLUE

MOUTH WASH

1 U.S. Gallon (128 FL.OZ.)